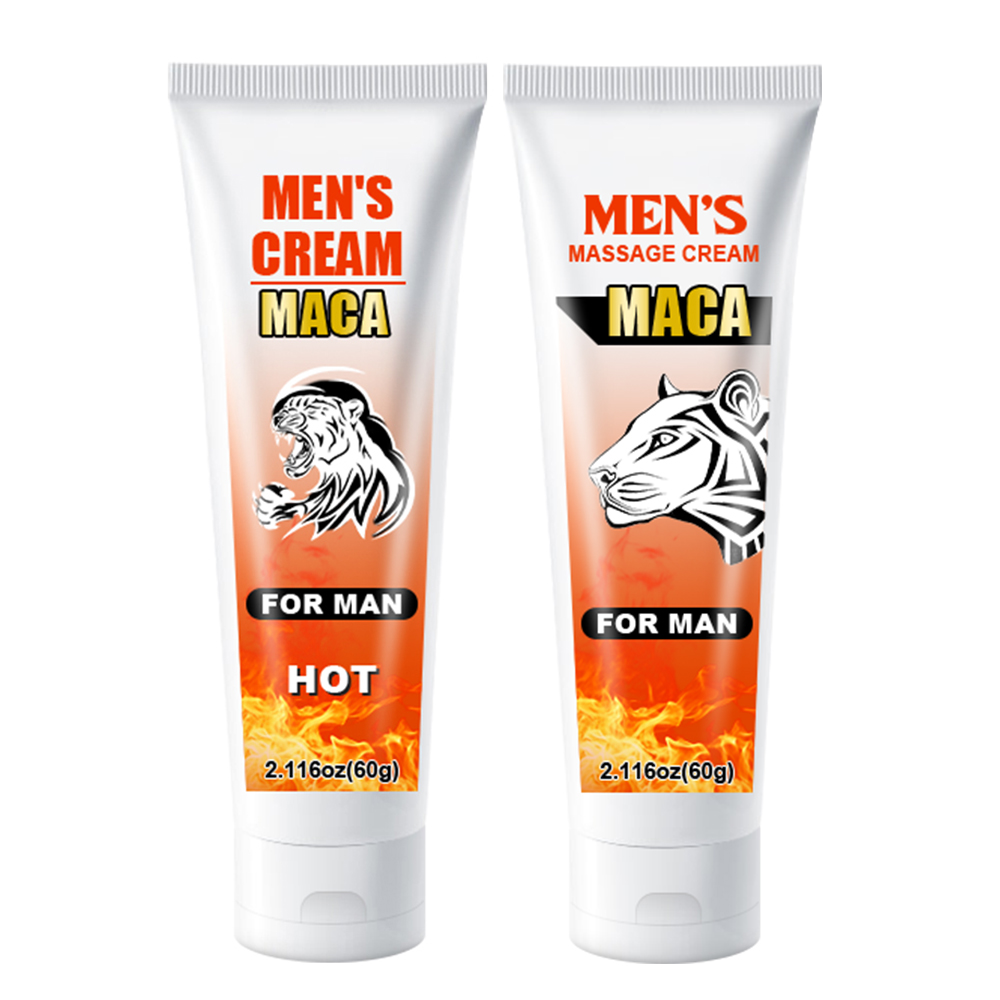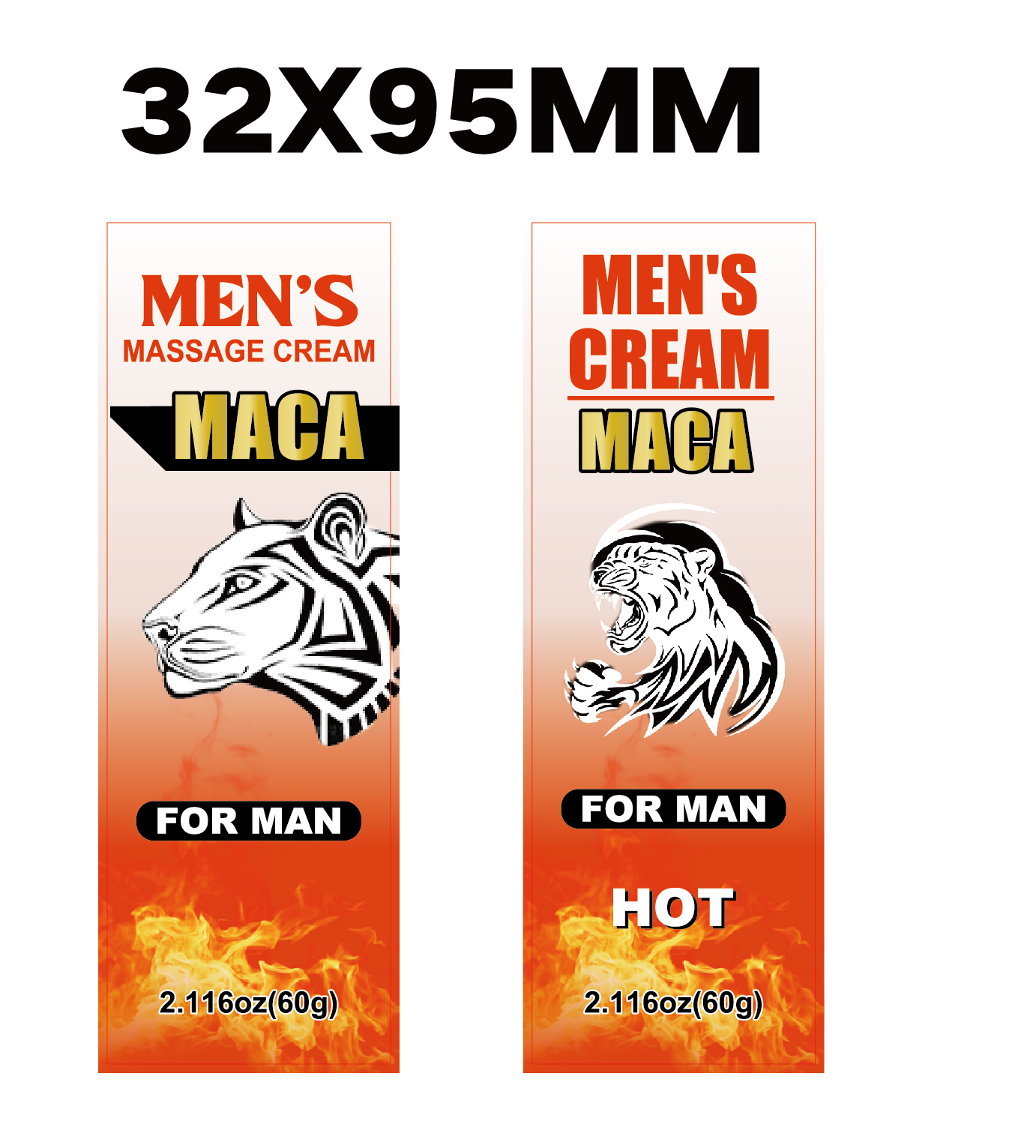 DRUG LABEL: Mens Massage Cream
NDC: 84025-205 | Form: CREAM
Manufacturer: Guangzhou Yanxi Biotechnology Co., Ltd
Category: otc | Type: HUMAN OTC DRUG LABEL
Date: 20241010

ACTIVE INGREDIENTS: PANTHENOL 3 mg/100 mL; GLYCERIN 5 mg/100 mL
INACTIVE INGREDIENTS: WATER

DOSAGE AND ADMINISTRATION

Apply to affected area twice per day on cleansed skin, Use continuously for 2-3 weeks for best results.

WARNINGS

keep out of children

INACTIVE INGREDIENT

Aqua

INDICATIONS AND USAGE

for man care

keep out of children

PURPOSE

for Thicker, Longer, Stronger Results